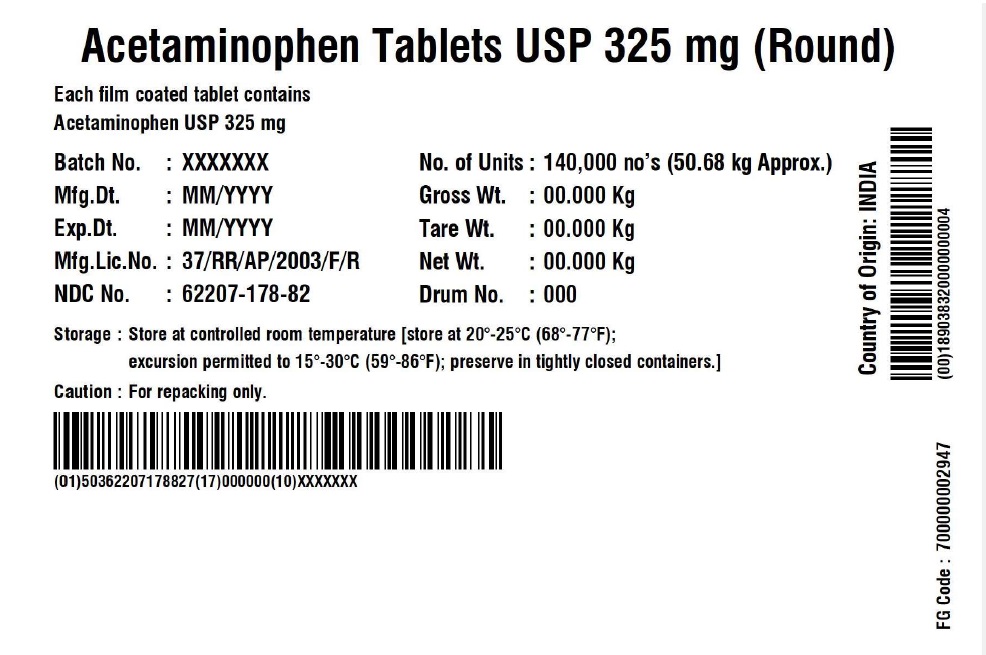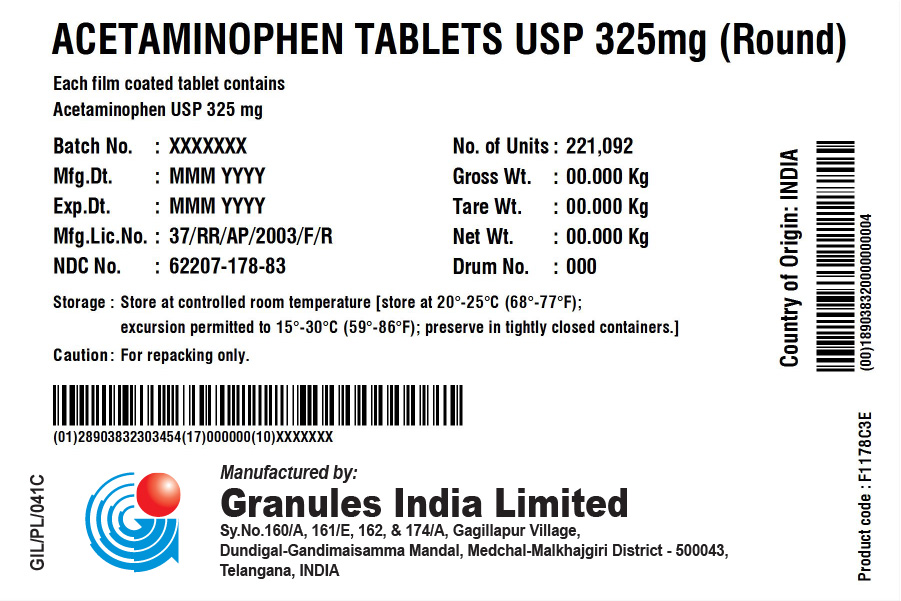 DRUG LABEL: Acetaminophen 325 mg
NDC: 62207-178 | Form: TABLET
Manufacturer: Granules India Limited
Category: otc | Type: HUMAN OTC DRUG LABEL
Date: 20230127

ACTIVE INGREDIENTS: ACETAMINOPHEN 325 mg/1 1
INACTIVE INGREDIENTS: HYPROMELLOSE, UNSPECIFIED; POLYETHYLENE GLYCOL, UNSPECIFIED; STARCH, CORN; SODIUM STARCH GLYCOLATE TYPE A POTATO; POVIDONE K30; STEARIC ACID

Acetaminophen tablets USP 325 mg (Round)